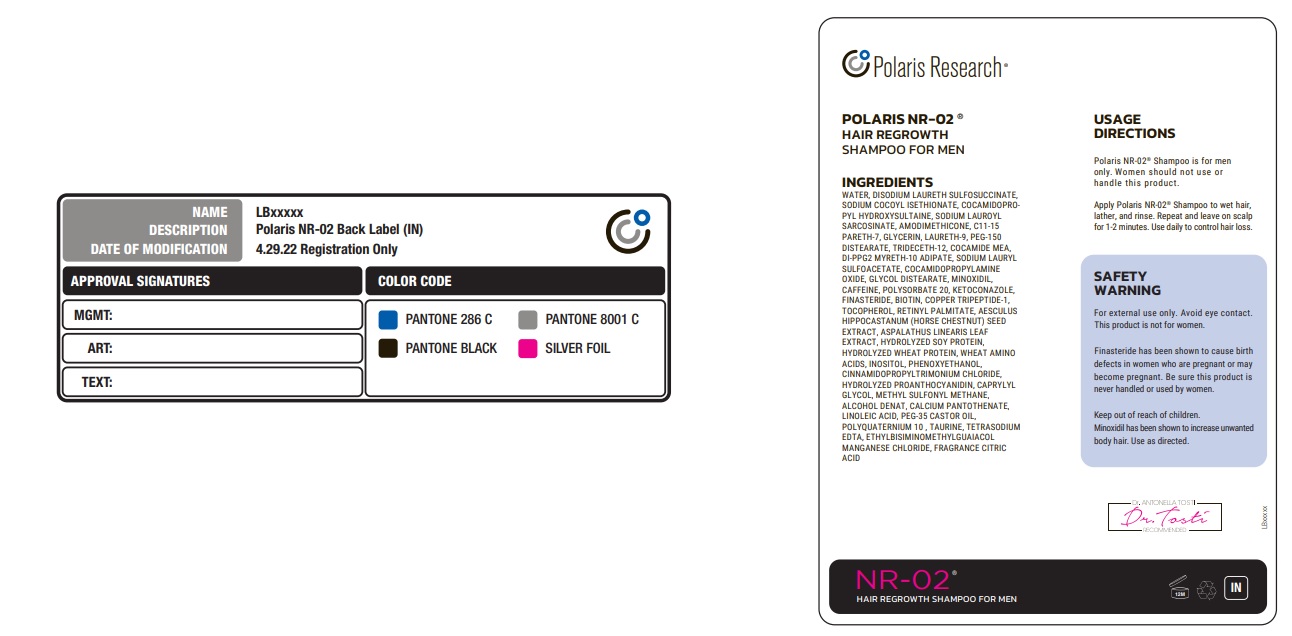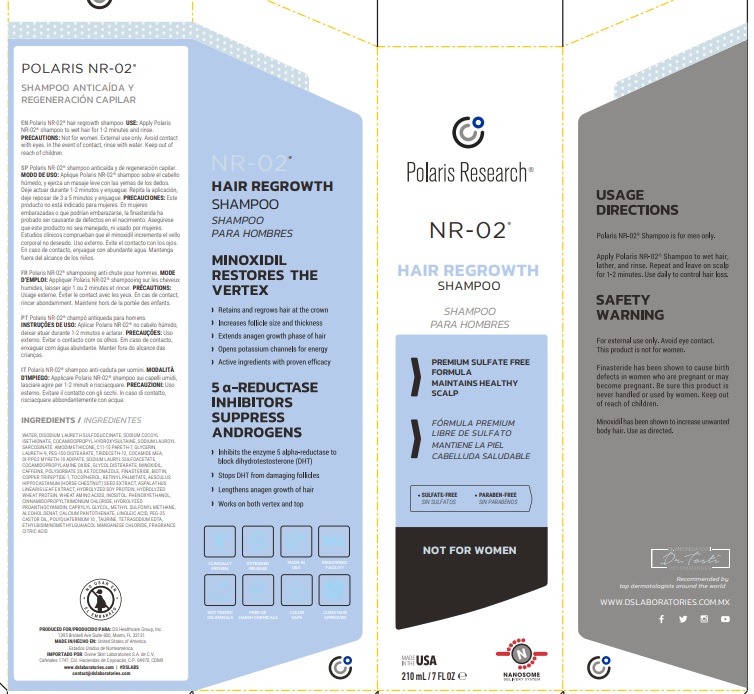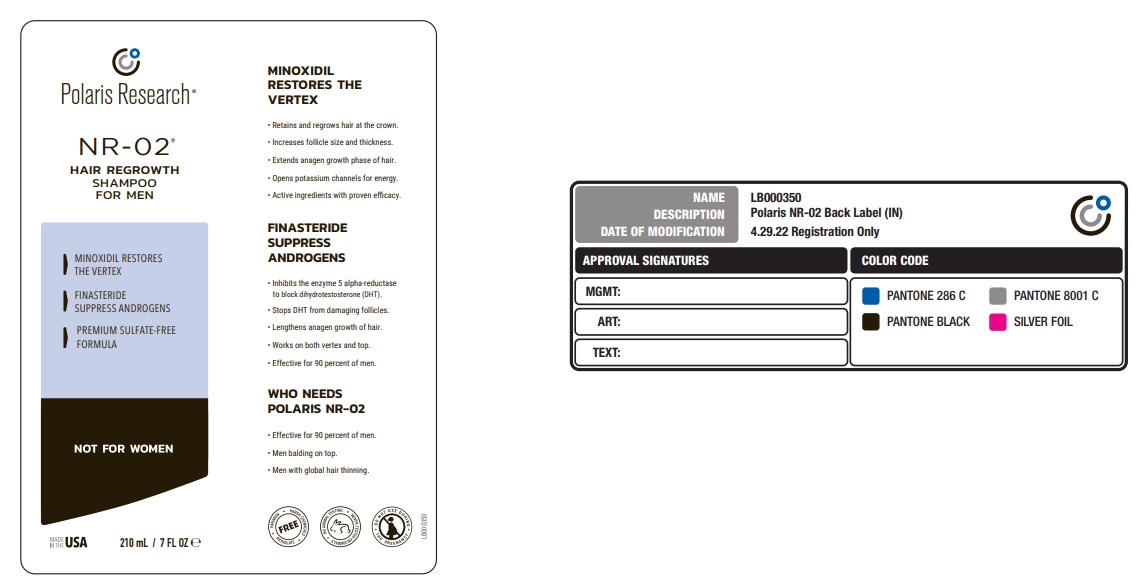 DRUG LABEL: Polaris Research NR-02 Hair Regrowth
NDC: 69188-400 | Form: SHAMPOO
Manufacturer: DS Healthcare Group
Category: otc | Type: HUMAN OTC DRUG LABEL
Date: 20230228

ACTIVE INGREDIENTS: MINOXIDIL 1.5 g/100 mL
INACTIVE INGREDIENTS: WATER; DISODIUM LAURETH SULFOSUCCINATE; SODIUM COCOYL ISETHIONATE; COCAMIDOPROPYL HYDROXYSULTAINE; SODIUM LAUROYL SARCOSINATE; AMODIMETHICONE (800 CST); C11-15 PARETH-7; GLYCERIN; POLIDOCANOL; PEG-150 DISTEARATE; TRIDECETH-12; COCO MONOETHANOLAMIDE; DI-PPG-2 MYRETH-10 ADIPATE; SODIUM LAURYL SULFOACETATE; COCAMIDOPROPYLAMINE OXIDE; GLYCOL DISTEARATE; CAFFEINE; POLYSORBATE 20; KETOCONAZOLE; FINASTERIDE; BIOTIN; PREZATIDE COPPER; TOCOPHEROL; VITAMIN A PALMITATE; HORSE CHESTNUT; ASPALATHUS LINEARIS LEAF; SOY PROTEIN; HYDROLYZED WHEAT PROTEIN (ENZYMATIC; 3000 MW); AMINO ACIDS, WHEAT; INOSITOL; PHENOXYETHANOL; ACETYLCYSTEINE SODIUM; PROCYANIDIN A2; CAPRYLYL GLYCOL; DIMETHYL SULFONE; ALCOHOL; CALCIUM PANTOTHENATE; LINOLEIC ACID; POLYOXYL 35 CASTOR OIL; POLYQUATERNIUM-10 (20000 MPA.S AT 2%); TAURINE; EDETATE SODIUM; ETHYLBISIMINOMETHYLGUAIACOL MANGANESE CHLORIDE; CITRIC ACID MONOHYDRATE

Polaris Research NR-02 Hair Regrowth Shampoo

Active ingredient

Minoxidil 1.5% W/W

PURPOSE

HAIR REGROWTH SHAMPOO FOR MEN

Use

Polaris NR-02® Shampoo is for men only. Women should not use or handle this product.

Warning

For external use only. Avoid eye contact. This product is not for women.Finasteride has been shown to cause birth defects in women who are pregnant or may become pregnant. Be sure this product is never handled or used by women.

Keep out of reach of children.
Minoxidil has been shown to increase unwanted body hair. Use as directed.

DIRECTIONS

Apply Polaris NR-02® Shampoo to wet hair, lather, and rinse. Repeat and leave on scalp for 1-2 minutes. Use daily to control hair loss.

Inactive ingredients

WATER, DISODIUM LAURETH SULFOSUCCINATE, SODIUM COCOYL ISETHIONATE, COCAMIDOPROPYL HYDROXYSULTAINE, SODIUM LAUROYL
SARCOSINATE, AMODIMETHICONE, C11-15 PARETH-7, GLYCERIN, LAURETH-9, PEG-150 DISTEARATE, TRIDECETH-12, COCAMIDE MEA,
DI-PPG2 MYRETH-10 ADIPATE, SODIUM LAURYL SULFOACETATE, COCAMIDOPROPYLAMINE OXIDE, GLYCOL DISTEARATE, MINOXIDIL,
CAFFEINE, POLYSORBATE 20, KETOCONAZOLE, FINASTERIDE, BIOTIN, COPPER TRIPEPTIDE-1,TOCOPHEROL, RETINYL PALMITATE, AESCULUS
HIPPOCASTANUM (HORSE CHESTNUT) SEED EXTRACT, ASPALATHUS LINEARIS LEAF EXTRACT, HYDROLYZED SOY PROTEIN,HYDROLYZED WHEAT PROTEIN, WHEAT AMINO ACIDS, INOSITOL, PHENOXYETHANOL,CINNAMIDOPROPYLTRIMONIUM CHLORIDE,HYDROLYZED PROANTHOCYANIDIN, CAPRYLYL GLYCOL, METHYL SULFONYL METHANE,ALCOHOL DENAT, CALCIUM PANTOTHENATE,LINOLEIC ACID, PEG-35 CASTOR OIL,
POLYQUATERNIUM 10 , TAURINE, TETRASODIUM EDTA, ETHYLBISIMINOMETHYLGUAIACOLMANGANESE CHLORIDE, FRAGRANCE CITRIC ACID